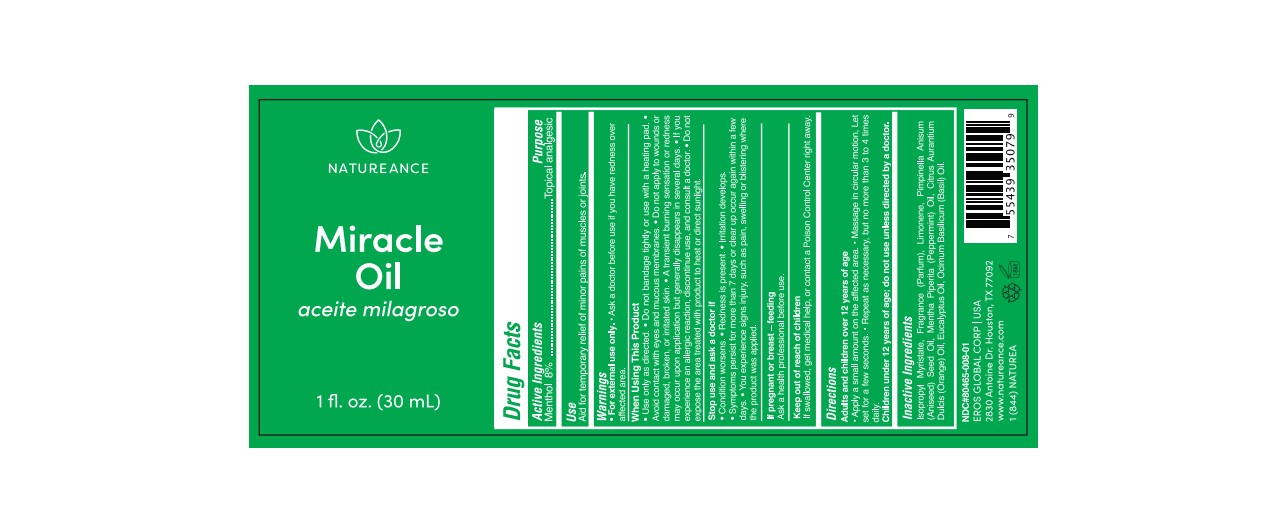 DRUG LABEL: NATUREANCE MIRACLE
NDC: 80465-008 | Form: OIL
Manufacturer: EROS GLOBAL CORP
Category: otc | Type: HUMAN OTC DRUG LABEL
Date: 20241023

ACTIVE INGREDIENTS: MENTHOL 8 g/100 g
INACTIVE INGREDIENTS: ISOPROPYL MYRISTATE; LIMONENE, (+)-

80465-008-01

ACTIVE INGREDIENT

Menthol 8%

PURPOSE

Topical Analgesic

USES:

Aid for temporary local relief of minor pain in muscles or joints.

WARNINGS

For external use only. · Ask a doctor before use if you have redness over affected area.

WHEN USING

Use only as directed.
Do not bandage tightly or use with a heating pad.
Avoid contact with eyes and mucous membranes.
Do not apply to wounds or damaged, broken, or irritated skin.
A transient burning sensation or redness may occur upon application but generally disappears in several days.
If you experience an allergic reaction, discontinue use, and consult a doctor.

Do not expose the area treated with product to heat or direct sunlight.

STOP USE

Condition worsens.
Redness is present.
Irritation develops.
Symptoms persist for more than 7 days or clear up occur again within a few days.

You experience signs injury, such as pain, swelling or blistering where the product was applied.

PREGNANCY OR BREAST FEEDING

Ask a health professional before use.

KEEP OUT OF REACH OF CHILDREN

If swallowed, get medical help or contact a Poison Control Center right away.

DIRECTIONS:

Adults and Children over 12 years of age

Apply a small amount on the affected area.
Massage in circular motion, Let set for a few seconds.
Repeat as necessary, but no more than 3 to 4 times daily.

Children under 12 years of age: do not use, consult a doctor.

INACTIVE INGREDIENT

Isopropyl Myristate, Fragrance (Parfum), Limonene, Pimpinella Anisum (Aniseed) Seed Oil, Mentha Piperita (Peppermint) Oil, Citrus Aurantium Dulcis (Orange) Oil, Eucalyptus Oil, Ocimum Basilicum (Basil) Oil.